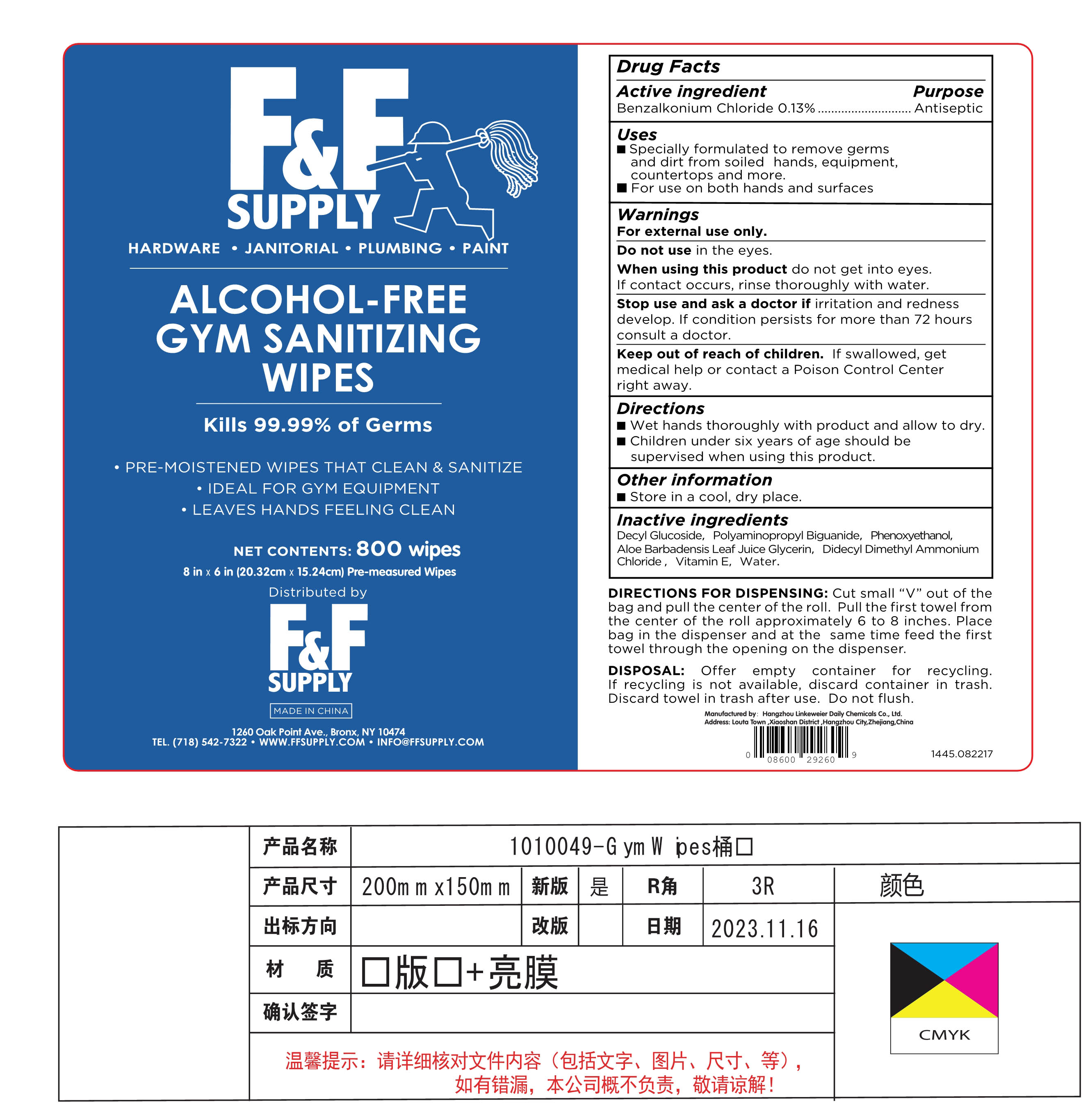 DRUG LABEL: ALCOHOL-FREE GYM SANITIZING WIPES
NDC: 71766-010 | Form: CLOTH
Manufacturer: Hangzhou Linkeweier Daily Chemicals Co., Ltd.
Category: otc | Type: HUMAN OTC DRUG LABEL
Date: 20231213

ACTIVE INGREDIENTS: BENZALKONIUM CHLORIDE 0.13 g/100 1
INACTIVE INGREDIENTS: DECYL GLUCOSIDE; POLYAMINOPROPYL BIGUANIDE; ALOE VERA LEAF; DIDECYLDIMONIUM CHLORIDE; WATER; PHENOXYETHANOL; .ALPHA.-TOCOPHEROL

71766-010

ACTIVE INGREDIENT

Benzalkonium Chloride 0.13%

PURPOSE

Antiseptic

INDICATIONS AND USAGE

Specially formulated to remove germs and dirt from soiled hands , equipment, countertops and more

For use on both hands and surfaces

WARNINGS

For external use only

Do not use in the eyes.

When using this product do not get into eyes .If contact occurs , rinse thoroughly with water.

Stop use and ask a doctor if irritation and redness develop If condition persists for more than 72 hours consult a doctor

Keep out of reach of children . If swallowed , get medical help or contact a Poison Control Center right away

DOSAGE AND ADMINISTRATION

Wet hands thoroughly with product and allow to dry.

Children under six years of age should be supervised when using this product

STORAGE AND HANDLING

Store in a cool , dry place

INACTIVE INGREDIENT

Decyl Glucoside , Polyaminopropyl Biguanide , Phenoxyethanol, Aloe Barbadensis Leaf Juice Glycerin , Didecyl Dimethyl Ammonium Chloride , Vitamin E, Water